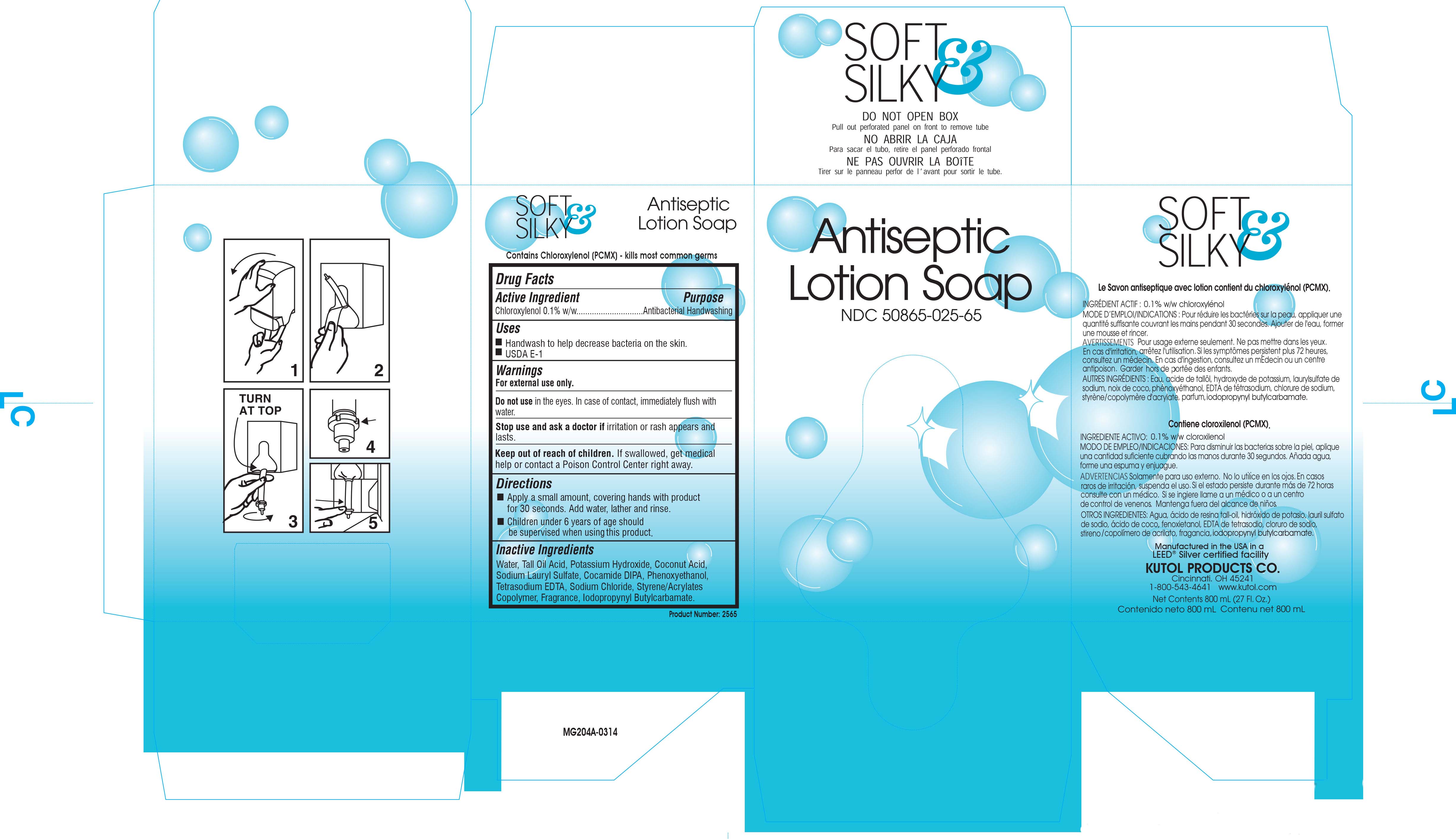 DRUG LABEL: Soft and Silky Antiseptic
NDC: 50865-025 | Form: SOLUTION
Manufacturer: Kutol Products Company, Inc.
Category: otc | Type: HUMAN OTC DRUG LABEL
Date: 20241218

ACTIVE INGREDIENTS: CHLOROXYLENOL 3.82 g/100 mL
INACTIVE INGREDIENTS: IODOPROPYNYL BUTYLCARBAMATE; SODIUM CHLORIDE; METHACRYLATE/METHOXY PEG-10 MALEATE/STYRENE COPOLYMER; FRAGRANCE FLORAL ORC0902236; WATER; EDETATE SODIUM; POTASSIUM HYDROXIDE; TALL OIL; COCONUT ACID; SODIUM LAURYL SULFATE; COCO DIISOPROPANOLAMIDE; PHENOXYETHANOL

F025F Soft and Silky Antiseptic

ACTIVE INGREDIENT

Chloroxylenol 0.1% w/w...........Antibacterial Handwashing

INACTIVE INGREDIENT

Water, Tall Oil Acid, Potassium Hydroxide, Coconut Acid, Sodium Lauryl Sulfate, Cocamide DIPA, Phenoxyethanol, Tetrasodium EDTA, Sodium Chloride, Styrene/Acrylates Copolymer, Fragrance, Iodopropynyl Butylcarbamate.

PURPOSE

Handwash to help decrease bacteria on the skin.

USDA E-1

WARNINGS

For external use only.

Do not use in the eyes. In case of contact, immediately flush with water.

Stop use and ask a doctor if irritation or rash appears and lasts.

Keep out of reach of children. If swallowed, get medical help or contact a Poison Control Center right away.

DOSAGE AND ADMINISTRATION

Apply a small amount, covering hands with product for 30 seconds. Add water, lather and rinse.

Children under 6 years of age should be supervised when using this product.

INDICATIONS AND USAGE

Handwash to help decrease bacteria on the skin.

USDA E-1

Do not use in the eyes. In case of contact, immediately flush with water.

Stop use and ask a doctor if irritation or redness appears and lasts.

Keep out of reach of children. If swallowed, get medical help or contact a Poison Control Center right away.

Keep out of reach of children. If swallowed, get medical help or contact a Poison Control Center right away.

PACKAGE LABEL

50865-025-65.jpg